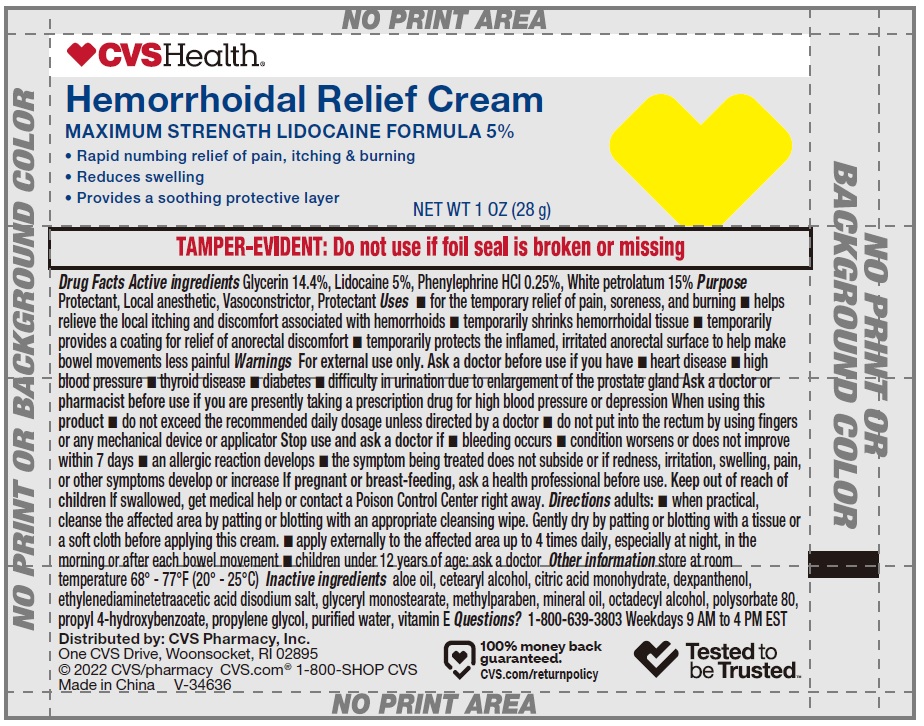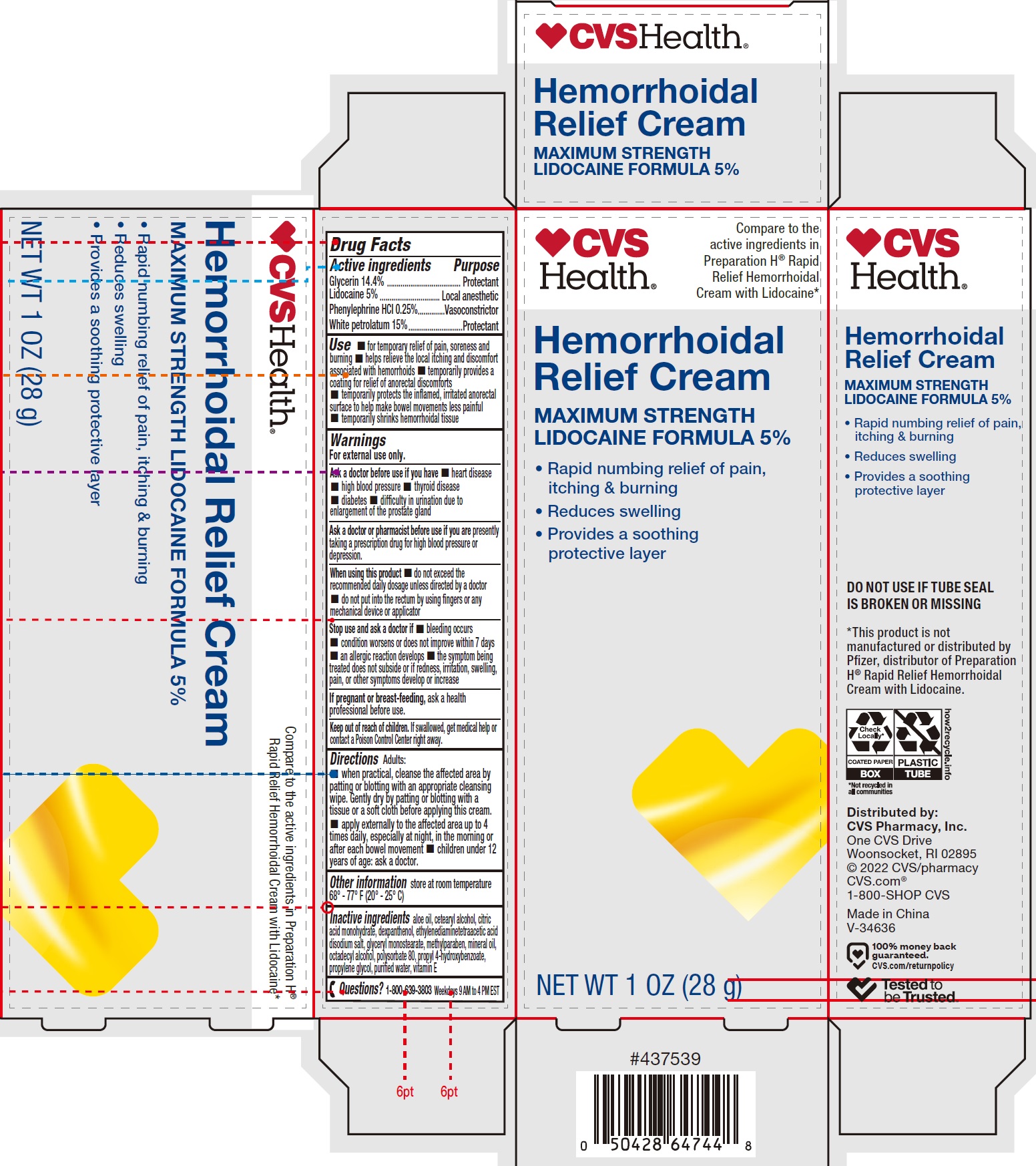 DRUG LABEL: HEMORRHOIDAL WITH LIDOCAINE
NDC: 51316-225 | Form: CREAM
Manufacturer: CVS PHARMACY, INC
Category: otc | Type: HUMAN OTC DRUG LABEL
Date: 20231024

ACTIVE INGREDIENTS: GLYCERIN 144 mg/1 g; LIDOCAINE 50 mg/1 g; PHENYLEPHRINE HYDROCHLORIDE 2.5 mg/1 g; WHITE PETROLATUM 150 mg/1 g
INACTIVE INGREDIENTS: CETOSTEARYL ALCOHOL; CITRIC ACID MONOHYDRATE; DEXPANTHENOL; GLYCERYL MONOSTEARATE; METHYLPARABEN; MINERAL OIL; STEARYL ALCOHOL; POLYSORBATE 80; PROPYLENE GLYCOL; WATER; .ALPHA.-TOCOPHEROL

HEMORRHOIDAL CREAM WITH LIDOCAINE

Active ingredients

Glycerin 14.4%

Lidocaine 5%

Phenylephrine HCl 0.25%

White petrolatum 15%

Purpose

Protectant

Local anesthetic

Vasoconstrictor

Protectant

Use

- for temporary relief of pain, soreness and burning
- helps relieve the local itching and discomfort associated with hemorrhoids
- temporarily provides a coating for relief of anorectal discomforts
- temporarily protects the inflamed, irritated anorectal surface to help make bowel movements less painful
- temporarily shrinks hemorrhoidal tissue

Warnings

For external use only.

Ask a doctor before use if you have

- heart disease
- high blood pressure
- thyroid disease
- diabetes
- diffficulty in urination due to enlargement of the prostate gland

Ask a doctor or pharmacist before use if you are

presently taking a prescription drug for high blood pressure or depression.

When using this product

- do not exceed the recommended daily dosage unless directed by a doctor
- do not put into the rectum by using fingers or any mechanical device or applicator

Stop use and ask a doctor if

- bleeding occurs
- condition worsens or does not improve within 7 days
- an allergic reaction develops
- the symptom being treated does not subside or if redness, irritation, swelling, pain, or other symptoms develop or increase

If pregnant or breast-feeding,

ask a health professional before use.

Keep out of reach of children.

If swallowed, get medical help or contact a Poison Control Center right away.

Directions

Adults:

- when practical, cleanse the affected area by patting or blotting with an appropriate cleansing wipe. Gently dry by patting or blotting with a tissue or a soft cloth before applying this cream.
- apply externally to the affected area up to 4 times daily, especially at night, in the morning or after each bowel movement
- children under 12 years of age: ask a doctor.

Other information

store at room temperature 68° - 77° F (20° - 25° C)

Inactive ingredients

aloe oil, cetearyl alcohol, citric acid monohydrate, dexpanthenol, ethylenediaminetetraacetic acid disodium salt, glyceryl monostearate, methylparaben, mineral oil, octadecyl alcohol, polysorbate 80, propyl 4-hydroxybenzoate, propylene glycol, purified water, vitamin E

Questions?

1-800-639-3803 Weekdays 9 AM to 4 PM EST